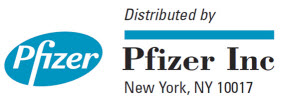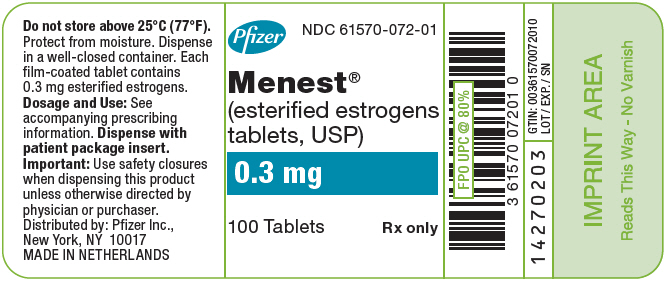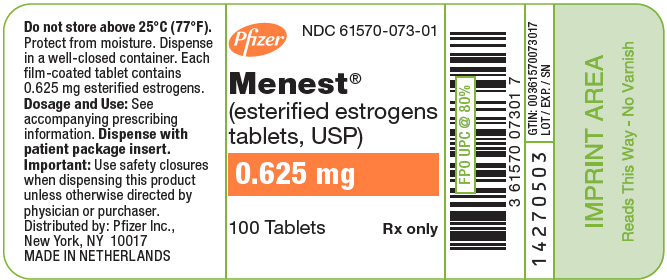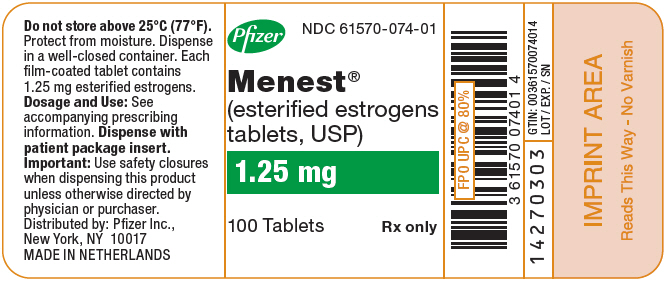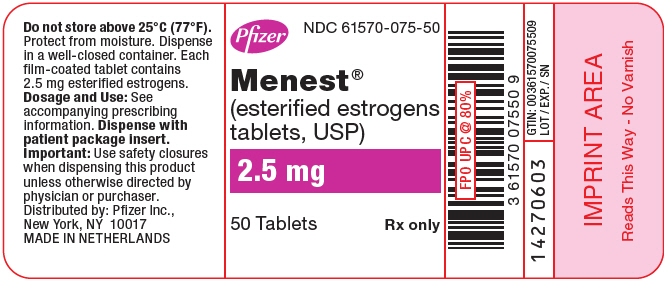 DRUG LABEL: MENEST
NDC: 61570-072 | Form: TABLET, FILM COATED
Manufacturer: Pfizer Laboratories Div Pfizer Inc
Category: prescription | Type: HUMAN PRESCRIPTION DRUG LABEL
Date: 20251111

ACTIVE INGREDIENTS: ESTROGENS, ESTERIFIED 0.3 mg/1 1
INACTIVE INGREDIENTS: ETHYLCELLULOSE, UNSPECIFIED; HYDROXYPROPYL CELLULOSE (1600000 WAMW); HYPROMELLOSE 2910 (15 MPA.S); LACTOSE, UNSPECIFIED FORM; MAGNESIUM STEARATE; METHYLCELLULOSE (15 MPA.S); POLYETHYLENE GLYCOL 300; SODIUM BICARBONATE; SHELLAC; STARCH, CORN; STEARIC ACID; TITANIUM DIOXIDE; VANILLIN; FD&C YELLOW NO. 6; D&C YELLOW NO. 10

MENEST®
(esterified estrogens tablets, USP)

Rx Only

BOXED WARNING

ESTROGENS INCREASE THE RISK OF ENDOMETRIAL CANCERt

Close clinical surveillance of all women taking estrogens is important. Adequate diagnostic measures, including endometrial sampling when indicated, should be undertaken to rule out malignancy in all cases of undiagnosed persistent or recurring abnormal vaginal bleeding. There is no evidence that the use of "natural" estrogens results in a different endometrial risk profile than synthetic estrogens at equivalent estrogen doses. (See WARNINGS, Malignant neoplasms, Endometrial cancer.)

CARDIOVASCULAR AND OTHER RISKS

Estrogens with and without progestins should not be used for the prevention of cardiovascular disease. (See WARNINGS, Cardiovascular disorders.)

The Women's Health Initiative (WHI) study reported increased risks of myocardial infarction, stroke, invasive breast cancer, pulmonary emboli, and deep vein thrombosis in postmenopausal women (50 to 79 years of age) during 5 years of treatment with oral conjugated estrogens (CE 0.625 mg) combined with medroxyprogesterone acetate (MPA 2.5 mg) relative to placebo (See CLINICAL PHARMACOLOGY , Clinical Studies .)

The Women's Health Initiative Memory Study (WHIMS), a substudy of WHI, reported increased risk of developing probable dementia in postmenopausal women 65 years of age or older during 4 years of treatment with oral conjugated estrogens plus medroxyprogesterone acetate relative to placebo. It is unknown whether this finding applies to younger postmenopausal women or to women taking estrogen alone therapy. (See CLINICAL PHARMACOLOGY, Clinical Studies.)

Other doses of conjugated estrogens with medroxyprogesterone acetate, and other combinations and dosage forms of estrogens and progestins were not studied in the WHI clinical trials and, in the absence of comparable data, these risks should be assumed to be similar. Because of these risks, estrogens with or without progestins should be prescribed at the lowest effective doses and for the shortest duration consistent with treatment goals and risks for the individual woman.

DESCRIPTION

Esterified estrogens is a mixture of the sodium salts of the sulfate esters of the estrogenic substances, principally estrone, that are of the type excreted by pregnant mares. It contains the concomitant component, 17α-estradiol. The content of total esterified estrogens is not less than 90 percent and not more than 110 percent of the labeled amount. Esterified estrogens contain not less than 75 percent and not more than 85 percent of sodium estrone sulfate, and not less than 6 percent and not more than 15 percent of sodium equilin sulfate, in such proportion that the total of these two components is not less than 90 percent, all percentages being calculated on the basis of the total esterified estrogens content.

Inactive Ingredients:

Ethyl cellulose, fragrances, hydroxypropyl cellulose, hypromellose 2910, lactose, magnesium stearate, methylcellulose, polyethylene glycol, sodium bicarbonate, shellac, starch, stearic acid, titanium dioxide, and vanillin. Dyes in the form of aluminum lakes are contained in each tablet strength as follows: 0.3 mg Tablet: FD&C Yellow No. 6, D&C Yellow No. 10. 0.625 mg Tablet: FD&C Yellow No. 6, D&C Yellow No. 10. 1.25 mg Tablet: FD&C Yellow No. 6, D&C Yellow No. 10, FD&C Blue No. 1. 2.5 mg Tablet: D&C Red No. 30.

CLINICAL PHARMACOLOGY

Endogenous estrogens are largely responsible for the development and maintenance of the female reproductive system and secondary sexual characteristics. Although circulating estrogens exist in a dynamic equilibrium of metabolic interconversions, estradiol is the principal intracellular human estrogen and is substantially more potent than its metabolites, estrone and estriol, at the receptor level.

The primary source of estrogen in normally cycling adult women is the ovarian follicle, which secrets 70 to 500 mcg of estradiol daily, depending on the phase of the menstrual cycle. After menopause, most endogenous estrogen is produced by conversion of androstenedione, secreted by the adrenal cortex, to estrone by the peripheral tissues. Thus, estrone and the sulfate conjugated form, estrone sulfate, are the most abundant circulating estrogens in postmenopausal women.

Estrogens act through binding to nuclear receptors in estrogen-responsive tissues. To date, two estrogen receptors have been identified. These vary in proportion from tissue to tissue.

Circulating estrogens modulate the pituitary secretion of the gonadotropins, luteinizing hormone (LH) and follicle stimulating hormone (FSH), through a negative feedback mechanism. Estrogens act to reduce the elevated levels of these hormones seen in postmenopausal women.

Distribution

The distribution of exogenous estrogens is similar to that of endogenous estrogens. Estrogens are widely distributed in the body and are generally found in higher concentrations in the sex hormone target organs. Estrogens circulate in the blood largely bound to sex hormone binding globulin (SHBG) and albumin.

Metabolism

Exogenous estrogens are metabolized in the same manner as endogenous estrogens. Circulating estrogens exist in a dynamic equilibrium of metabolic interconversions. These transformations take place mainly in the liver. Estradiol is converted reversibly to estrone, and both can be converted to estriol, which is the major urinary metabolite. Estrogens also undergo enterohepatic recirculation via sulfate and glucuronide conjugation in the liver, biliary secretion of conjugates into the intestine, and hydrolysis in the gut followed by reabsorption. In postmenopausal women, a significant proportion of the circulating estrogens exist as sulfate conjugates, especially estrone sulfate, which serves as a circulating reservoir for the formulation of more active estrogens.

Excretion

Estradiol, estrone, and estriol are excreted in the urine along with glucuronide and sulfate conjugates.

Drug Interactions

In vitro and in vivo studies have shown that estrogens are metabolized partially by cytochrome P450 3A4 (CYP3A4). Therefore, inducers or inhibitors of CYP3A4 may affect estrogen drug metabolism. Inducers of CYP3A4 such as St. John's Wort preparations (Hypericum perforatum), phenobarbital, carbamazepine, and rifampin may reduce plasma concentrations of estrogens, possibly resulting in a decrease in therapeutic effects and/or changes in the uterine bleeding profile. Inhibitors of CYP3A4 such as erythromycin, clarithromycin, ketoconazole, itraconazole, ritonavir and grapefruit juice may increase plasma concentrations of estrogens and may result in side effects.

Clinical Studies

Women's Health Initiative Studies

The Women's Health Initiative (WHI) enrolled a total of 27,000 predominantly healthy postmenopausal women to assess the risks and benefits of either the use of oral 0.625 mg conjugated estrogens (CE) per day alone or the use of oral 0.625 mg conjugated estrogens plus 2.5 mg medroxyprogesterone acetate (MPA) per day compared to placebo in the prevention of certain chronic diseases. The primary endpoint was the incidence of coronary heart disease (CHD) (nonfatal myocardial infarction and CHD death), with invasive breast cancer as the primary adverse outcome studied. A "global index" included the earliest occurrence of CHD, invasive breast cancer, stroke, pulmonary embolism (PE), endometrial cancer, colorectal cancer, hip fracture, or death due to other cause. The study did not evaluate the effects of CE or CE/MPA on menopausal symptoms.

The CE/MPA substudy was stopped early because, according to the predefined stopping rule, the increased risk of breast cancer and cardiovascular events exceeded the specified benefits included in the "global index." Results of the CE/MPA substudy, which included 16,608 women (average age of 63 years, range 50 to 79; 83.9% White, 6.5% Black, 5.5% Hispanic), after an average follow-up of 5.2 years are presented in Table 1 below:

Table 1. RELATIVE AND ABSOLUTE RISK SEEN IN THE CE/MPA SUBSTUDY OF WHI [adapted from JAMA, 2002; 288:321–333]
Event [a subset of the events was combined in a "global index", defined as the earliest occurrence of CHD events, invasive breast cancer, stroke, pulmonary embolism, endometrial cancer, colorectal cancer, hip fracture, or death due to other causes] | Relative Risk CE/MPA vs placebo at 5.2 Years (95% CI [nominal confidence intervals unadjusted for multiple looks and multiple comparisons]) | Placebo n = 8102 | CE/MPA n = 8506
 |  | Absolute Risk per 10,000 Person-years
CHD events | 1.29 (1.02–1.63) | 30 | 37
Non-fatal MI | 1.32 (1.02–1.72) | 23 | 30
CHD death | 1.18 (0.70–1.97) | 6 | 7
Invasive breast cancer [includes metastatic and non-metastatic breast cancer with the exception of in situ breast cancer] | 1.26 (1.00–1.59) | 30 | 38
Stroke | 1.41 (1.07–1.85) | 21 | 29
Pulmonary embolism | 2.13 (1.39–3.25) | 8 | 16
Colorectal cancer | 0.63 (0.43–0.92) | 16 | 10
Endometrial cancer | 0.83 (0.47–1.47) | 6 | 5
Hip fracture | 0.66 (0.45–0.98) | 15 | 10
Death due to causes other than the events above | 0.92 (0.74–1.14) | 40 | 37
Global Index | 1.15 (1.03–1.28) | 151 | 170
Deep vein thrombosis [not included in Global Index] | 2.07 (1.49–2.87) | 13 | 26
Vertebral fractures | 0.66 (0.44–0.98) | 15 | 9
Other osteoporotic fractures | 0.77 (0.69–0.86) | 170 | 131

For those outcomes included in the "global index," absolute excess risks per 10,000 women-years in the group treated with CE/MPA were 7 more CHD events, 8 more strokes, 8 more PEs, and 8 more invasive breast cancers, while absolute risk reductions per 10,000 women-years were 6 fewer colorectal cancers and 5 fewer hip fractures. The absolute excess risk of events included in the "global index" was 19 per 10,000 women-years. There was no difference between the groups in terms of all-cause mortality. (See Boxed Warning, WARNINGS, and PRECAUTIONS.)

Women's Health Initiative Memory Study

The Women's Health Initiative Memory Study (WHIMS), a substudy of WHI, enrolled 4,532 predominantly healthy postmenopausal women 65 years of age and older (47% were age 65 to 69 years, 35% were 70 to 74 years, and 18% were 75 years of age and older) to evaluate the effects of CE/MPA (0.625 mg conjugated estrogens plus 2.5 mg medroxyprogesterone acetate) on the incidence of probable dementia (primary outcome) compared with placebo. After an average follow-up of 4 years, 40 women in the estrogen/progestin group (45 per 10,000 women-years) and 21 in the placebo group (22 per 10,000 women-years) were diagnosed with probable dementia. The relative risk of probable dementia in the hormone therapy group was 2.05 (95% CI, 1.21 to 3.48) compared to placebo. Differences between groups became apparent in the first year of treatment. It is unknown whether these findings apply to younger postmenopausal women. (See Boxed Warning and WARNINGS, Dementia.)

INDICATIONS AND USAGE

Menest is indicated in the:

1. Treatment of moderate to severe vasomotor symptoms associated with the menopause.
2. Treatment of moderate to severe symptoms of vulvar and vaginal atrophy associated with the menopause. When prescribing solely for the treatment of symptoms of vulvar and vaginal atrophy, topical vaginal products should be considered.
3. Female hypogonadism.
4. Female castration.
5. Primary ovarian failure.
6. Breast cancer (for palliation only) in appropriately selected women and men with metastatic disease.
7. Prostatic carcinoma - palliative therapy of advanced disease.

CONTRAINDICATIONS

Menest should not be used in women with any of the following conditions:

1. Undiagnosed abnormal genital bleeding.
2. Known, suspected, or history of cancer of the breast except in appropriately selected patients being treated for metastatic disease.
3. Known or suspected estrogen-dependent neoplasia.
4. Active deep vein thrombosis, pulmonary embolism or a history of these conditions.
5. Active or recent (e.g., within the past year) arterial thromboembolic disease (e.g., stroke, myocardial infarction).
6. Liver dysfunction or disease.
7. Menest should not be used in patients with known hypersensitivity to its ingredients.
8. Known or suspected pregnancy. There is no indication for Menest in pregnancy. There appears to be little or no increased risk of birth defects in children born to women who have used estrogens and progestins from oral contraceptives inadvertently during early pregnancy. (See PRECAUTIONS.)

WARNINGS

See Boxed Warnings.

The use of unopposed estrogens in women who have a uterus is associated with an increased risk of endometrial cancer.

1. Cardiovascular disorders

Estrogen and estrogen/progestin therapy has been associated with an increased risk of cardiovascular events such as myocardial infarction and stroke, as well as venous thrombosis and pulmonary embolism (venous thromboembolism or VTE). Should any of these occur or be suspected, estrogens should be discontinued immediately.

Risk factors for arterial vascular disease (e.g., hypertension, diabetes mellitus, tobacco use, hypercholesterolemia, and obesity) and/or venous thromboembolism (e.g., personal history or family history of VTE, obesity, and systemic lupus erythematosus) should be managed appropriately.

a. Coronary heart disease and stroke

In the Women's Health Initiative study (WHI), an increase in the number of myocardial infarctions and strokes has been observed in women receiving CE compared to placebo. These observations are preliminary. (See CLINICAL PHARMACOLOGY, Clinical Studies.)

In the CE/MPA substudy of WHI, an increased risk of coronary heart disease (CHD) events (defined as nonfatal myocardial infarction and CHD death) was observed in women receiving CE/MPA compared to women receiving placebo (37 vs 30 per 10,000 women-years). The increase in risk was observed in year one and persisted.

In the same substudy of WHI, an increased risk of stroke was observed in women receiving CE/MPA compared to women receiving placebo (29 vs 21 per 10,000 women-years). The increase in risk was observed after the first year and persisted.

In postmenopausal women with documented heart disease (n = 2,763, average age 66.7 years) a controlled clinical trial of secondary prevention of cardiovascular disease (Heart and Estrogen/Progestin Replacement study; HERS) treatment with CE/MPA (0.625mg/2.5mg per day) demonstrated no cardiovascular benefit. During an average follow-up of 4.1 years, treatment with CE/MPA did not reduce the overall rate of CHD events in postmenopausal women with established coronary heart disease. There were more CHD events in the CE/MPA-treated group than in the placebo group in year 1, but not during the subsequent years. Two thousand three hundred and twenty-one women from the original HERS trial agreed to participate in an open label extension of HERS, HERS II. Average follow-up in HERS II was an additional 2.7 years, for a total of 6.8 years overall. Rates of CHD events were comparable among women in the CE/MPA group and the placebo group in HERS, HERS II and overall.

Large doses of estrogen (5 mg conjugated estrogens per day), comparable to those used to treat cancer of the prostate and breast, have been shown in a large prospective clinical trial in men to increase the risks of nonfatal myocardial infarction, pulmonary embolism, and thrombophlebitis.

b. Venous thromboembolism (VTE)

In the Women's Health Initiative study (WHI), an increase in VTE has been observed in women receiving CE compared to placebo. These observations are preliminary. (See CLINICAL PHARMACOLOGY, Clinical Studies.)

In the CE/MPA substudy of WHI, a 2-fold greater rate of VTE, including deep venous thrombosis and pulmonary embolism, was observed in women receiving CE/MPA compared to women receiving placebo. The rate of VTE was 34 per 10,000 women-years in the CE/MPA group compared to 16 per 10,000 women-years in the placebo group. The increase in VTE risk was observed during the first year and persisted.

If feasible, estrogens should be discontinued at least 4 to 6 weeks before surgery of the type associated with an increased risk of thromboembolism, or during periods of prolonged immobilization.

2. Malignant neoplasms

a. Endometrial cancer

The use of unopposed estrogens in women with intact uteri has been associated with an increased risk of endometrial cancer. The reported endometrial cancer risk among unopposed estrogen users is about 2- to 12- fold greater than in non-users, and appears dependent on duration of treatment and on estrogen dose. Most studies show no significant increased risk associated with use of estrogens for less than one year. The greatest risk appears associated with prolonged use, with increased risks of 15- to 24-fold for five to ten years or more and this risk has been shown to persist for at least 8 to 15 years after estrogen therapy is discontinued.

Clinical surveillance of all women taking estrogen/progestin combinations is important. Adequate diagnostic measures, including endometrial sampling when indicated, should be undertaken to rule out malignancy in all cases of undiagnosed persistent or recurring abnormal vaginal bleeding. There is no evidence that the use of natural estrogens results in a different endometrial risk profile than synthetic estrogens, of equivalent estrogen dose. Adding a progestin to estrogen therapy has been shown to reduce the risk of endometrial hyperplasia, which may be a precursor to endometrial cancer.

b. Breast cancer

The most important randomized clinical trial providing information about breast cancer in estrogen plus progestin users is the WHI substudy of daily CE (0.625 mg) plus MPA (2.5 mg). After a mean follow-up of 5.6 years the estrogen plus progestin substudy reported an increased risk of invasive breast cancer in women who took daily CE plus MPA. In this substudy, prior use of estrogen‑alone or estrogen plus progestin therapy was reported by 26 percent of the women. The relative risk of invasive breast cancer was 1.24 and the absolute risk was 41 versus 33 cases per 10,000 women-years, for CE plus MPA compared with placebo. Among women who reported prior use of hormone therapy, the relative risk of invasive breast cancer was 1.86, and the absolute risk was 46 versus 25 cases per 10,000 women-years, for CE plus MPA compared with placebo. Among women who reported no prior use of hormone therapy, the relative risk of invasive breast cancer was 1.09, and the absolute risk was 40 versus 36 cases per 10,000 women-years for CE plus MPA compared with placebo. In the same substudy, invasive breast cancers were larger, were more likely to be node positive, and were diagnosed at a more advanced stage in the CE (0.625 mg) plus MPA (2.5 mg) group compared with the placebo group. Metastatic disease was rare with no apparent difference between the two groups. Other prognostic factors such as histologic subtype, grade and hormone receptor status did not differ between the groups.

The most important randomized clinical trial providing information about breast cancer in estrogen-alone users is the WHI substudy of daily CE (0.625 mg)-alone. In the WHI estrogen‑alone substudy, after an average follow-up of 7.1 years, daily CE (0.625 mg)-alone was not associated with an increased risk of invasive breast cancer [relative risk (RR) 0.80].

Consistent with the Women’s Health Initiative (WHI clinical trials), observational studies have also reported an increased risk of breast cancer for estrogen plus progestin therapy and a smaller, but still increased risk, for estrogen-alone therapy after several years of use. One large meta‑analysis of prospective cohort studies reported increased risks that were dependent upon duration of use and could last up to >10 years after discontinuation of estrogen plus progestin therapy and estrogen-alone therapy. Extension of the WHI trials also demonstrated increased breast cancer risk associated with estrogen plus progestin therapy. Observational studies also suggest that the risk of breast cancer was greater, and became apparent earlier, with estrogen plus progestin therapy as compared to the risk with estrogen-alone therapy. However, these studies have not found significant variation in the risk of breast cancer among different estrogen plus progestin combinations, doses, or routes of administration.

The use of estrogen-alone and estrogen plus progestin have been reported to result in an increase in abnormal mammograms requiring further evaluation.

All women should receive yearly breast examinations by a healthcare provider and perform monthly breast self-examinations. In addition, mammography examinations should be scheduled based on patient age, risk factors, and prior mammogram results.

3. Dementia

In the Women's Health Initiative Memory Study (WHIMS), 4,532 generally healthy postmenopausal women 65 years of age and older were studied, of whom 35% were 70 to 74 years of age and 18% were 75 or older. After an average follow-up of 4 years, 40 women being treated with CE/MPA (1.8%, n = 2,229) and 21 women in the placebo group (0.9%, n = 2,303) received diagnoses of probable dementia. The relative risk for CE/MPA versus placebo was 2.05 (95% confidence interval 1.21 – 3.48), and was similar for women with and without histories of menopausal hormone use before WHIMS. The absolute risk of probable dementia for CE/MPA versus placebo was 45 versus 22 cases per 10,000 women-years, and the absolute excess risk for CE/MPA was 23 cases per 10,000 women-years.

It is unknown whether these findings apply to younger postmenopausal women. (See CLINICAL PHARMACOLOGY, Clinical Studies and PRECAUTIONS, GERIATRIC USE.)

It is unknown whether these findings apply to estrogen alone therapy.

4. Gallbladder disease

A 2- to 4-fold increase in the risk of gallbladder disease requiring surgery in postmenopausal women receiving estrogens has been reported.

5. Hypercalcemia

Estrogen administration may lead to severe hypercalcemia in patients with breast cancer and bone metastases. If hypercalcemia occurs, use of the drug should be stopped and appropriate measures taken to reduce the serum calcium level.

6. Visual abnormalities

Retinal vascular thrombosis has been reported in patients receiving estrogens. Discontinue medication pending examination if there is a sudden partial or complete loss of vision, or a sudden onset of proptosis, diplopia, or migraine. If examination reveals papilledema or retinal vascular lesions, estrogens should be permanently discontinued.

7. Hepatic adenoma

Benign hepatic adenomas appear to be associated with the use of oral contraceptives. Although benign, and rare, these may rupture and may cause death through intra-abdominal hemorrhage. Such lesions have not yet been reported in association with other estrogen or progestagen preparations but should be considered in estrogen users having abdominal pain and tenderness, abdominal mass, or hypovolemic shock. Hepatocellular carcinoma has also been reported in women taking estrogen-containing oral contraceptives. The relationship of this malignancy to these drugs is not known at this time.

PRECAUTIONS

A. GENERAL

1. Addition of a progestin when a woman has not had a hysterectomy

Studies of the addition of progestin for 10 or more days of a cycle of estrogen administration, or daily with estrogen in a continuous regimen, have reported a lowered incidence of endometrial hyperplasia than would be induced by estrogen treatment alone. Endometrial hyperplasia may be a precursor to endometrial cancer.

There are, however, possible risks that may be associated with the use of progestins with estrogens compared to estrogen-alone regimens. These include a possible increased risk of breast cancer.

2. Elevated blood pressure

In a small number of case reports, substantial increases in blood pressure have been attributed to idiosyncratic reactions to estrogens. In a large, randomized, placebo-controlled clinical trial, a generalized effect of estrogens on blood pressure was not seen. Blood pressure should be monitored at regular intervals with estrogen use.

3. Hypertriglyceridemia

In patients with pre-existing hypertriglyceridemia, estrogen therapy may be associated with elevations of plasma triglycerides leading to pancreatitis and other complications.

4. Impaired liver function and past history of cholestatic jaundice

Estrogens may be poorly metabolized in patients with impaired liver function. For patients with a history of cholestatic jaundice associated with past estrogen use or with pregnancy, caution should be exercised and in the case of recurrence, medication should be discontinued.

5. Hypothyroidism

Estrogen administration leads to increased thyroid-binding globulin (TBG) levels. Patients with normal thyroid function can compensate for the increased TBG by making more thyroid hormone, thus maintaining free T4 and T3 serum concentrations in the normal range. Patients dependent on thyroid hormone replacement therapy who are also receiving estrogens may require increased doses of their thyroid replacement therapy. These patients should have their thyroid function monitored in order to maintain their free thyroid hormone levels in an acceptable range.

6. Fluid retention

Because estrogens may cause some degree of fluid retention, patients with conditions that might be influenced by this factor, such as a cardiac or renal dysfunction, warrant careful observation when estrogens are prescribed.

7. Hypocalcemia

Estrogens should be used with caution in individuals with severe hypocalcemia.

8. Ovarian cancer

The CE/MPA substudy of WHI reported that estrogen plus progestin increased the risk of ovarian cancer. After an average follow-up of 5.6 years, the relative risk for ovarian cancer for CE/MPA versus placebo was 1.58 (95% confidence interval 0.77 – 3.24) but was not statistically significant. The absolute risk for CE/MPA versus placebo was 4.2 versus 2.7 cases per 10,000 women-years. In some epidemiologic studies, the use of estrogen alone, in particular for ten or more years, has been associated with an increased risk of ovarian cancer. Other epidemiologic studies have not found these associations.

9. Exacerbation of endometriosis

Endometriosis may be exacerbated with administration of estrogens. A few cases of malignant transformation of residual endometrial implants have been reported in women treated post-hysterectomy with estrogen alone therapy. For patients known to have residual endometriosis post-hysterectomy, the addition of progestin should be considered.

10. Exacerbation of other conditions

Estrogens may cause an exacerbation of asthma, diabetes mellitus, epilepsy, migraine or porphyria, systemic lupus erythematosus, and hepatic hemangiomas and should be used with caution in women with these conditions.

B. PATIENT INFORMATION

Physicians are advised to discuss the PATIENT INFORMATION leaflet with patients for whom they prescribe Menest.

C. LABORATORY TESTS

Estrogen administration should be initiated at the lowest dose approved for the indication and then guided by clinical response, rather than by serum hormone levels (e.g., estradiol, FSH).

D. DRUG/LABORATORY TEST INTERACTIONS

1. Accelerated prothrombin time, partial thromboplastin time, and platelet aggregation time; increased platelet count; increased factors II, VII antigen, VIII antigen, VIII coagulant activity; IX, X, XII, VII-X complex, II-VII-X complex, and beta-thromboglobulin; decreased levels of antifactor Xa and antithrombin III, decreased antithrombin III activity; increased levels of fibrinogen and fibrinogen activity; increased plasminogen antigen and activity.
2. Increased thyroid-binding globulin (TBG) levels leading to increased circulating total thyroid hormone levels as measured by protein-bound iodine (PBI), T4 levels (by column or by radioimmunoassay) or T3 levels by radioimmunoassay. T3 resin uptake is decreased, reflecting the elevated TBG. Free T4 and free T3 concentrations are unaltered. Patients on thyroid replacement therapy may require higher doses of thyroid hormone.
3. Other binding proteins may be elevated in serum (i.e., corticosteroid binding globulin (CBG), sex hormone binding globulin (SHBG)) leading to increased total circulating corticosteroids and sex steroids, respectively. Free hormone concentrations may be decreased. Other plasma proteins may be increased (angiotensinogen/renin substrate, alpha-1-antitrypsin, ceruloplasmin).
4. Increased plasma HDL and HDL2 cholesterol subfraction concentrations, reduced LDL cholesterol concentration, increased triglycerides levels.
5. Impaired glucose tolerance.
6. Reduced response to metyrapone test.

E. CARCINOGENESIS, MUTAGENESIS, AND IMPAIRMENT OF FERTILITY

Long-term continuous administration of estrogen, with and without progestin, in women with and without a uterus, has shown an increased risk of endometrial cancer, breast cancer, and ovarian cancer. (See Boxed Warning, WARNINGS and PRECAUTIONS.)

Long-term continuous administration of natural and synthetic estrogens in certain animal species increases the frequency of carcinomas of the breast, uterus, cervix, vagina, testis, and liver.

F. PREGNANCY

Menest should not be used during pregnancy. (See CONTRAINDICATIONS.)

G. NURSING MOTHERS

Estrogen administration to nursing mothers has been shown to decrease the quantity and quality of the milk. Detectable amounts of estrogens have been identified in the milk of mothers receiving this drug. Caution should be exercised when Menest is administered to a nursing mother.

H. PEDIATRIC USE

Safety and effectiveness in pediatric patients have not been established.

I. GERIATRIC USE

In the Women's Health Initiative Memory Study, including 4,532 women 65 years of age and older, followed for an average of 4 years, 82% (n = 3,729) were 65 to 74 while 18% (n = 803) were 75 and over. Most women (80%) had no prior hormone therapy use. Women treated with conjugated estrogens plus medroxyprogesterone acetate were reported to have a two-fold increase in the risk of developing probable dementia. Alzheimer's disease was the most common classification of probable dementia in both the conjugated estrogens plus medroxyprogesterone acetate group and the placebo group. Ninety percent of the cases of probable dementia occurred in the 54% of women that were older than 70. (See WARNINGS, Dementia.)

It is unknown whether these findings apply to estrogen alone therapy.

ADVERSE REACTIONS

See Boxed Warnings, WARNINGS and PRECAUTIONS .

The following additional adverse reactions have been reported with estrogens and/or progestin therapy.

1. Genitourinary system

Changes in vaginal bleeding pattern and abnormal withdrawal bleeding or flow; breakthrough bleeding; spotting; dysmenorrhea, increase in size of uterine leiomyomata; vaginitis, including vaginal candidiasis; change in amount of cervical secretion; changes in cervical ectropion; ovarian cancer; endometrial hyperplasia; endometrial cancer; premenstrual like syndrome, amenorrhea during and after treatment; cystitis like syndrome.

2. Breasts

Tenderness, enlargement, pain, nipple discharge, galactorrhea; fibrocystic breast changes; breast cancer.

3. Cardiovascular

Deep and superficial venous thrombosis; pulmonary embolism; thrombophlebitis; myocardial infarction; stroke; increase in blood pressure.

4. Gastrointestinal

Nausea, vomiting; abdominal cramps, bloating; cholestatic jaundice; increased incidence of gall bladder disease; pancreatitis, enlargement of hepatic hemangiomas.

5. Skin

Chloasma or melasma, that may persist when drug is discontinued; erythema multiforme; erythema nodosum; hemorrhagic eruption; loss of scalp hair; hirsutism; pruritus, rash.

6. Eyes

Retinal vascular thrombosis; steepening of corneal curvature; intolerance to contact lenses.

7. Central nervous system

Headache; migraine; dizziness; mental depression; chorea; nervousness; mood disturbances; irritability; exacerbation of epilepsy, dementia.

8. Miscellaneous

Increase or decrease in weight; reduced carbohydrate tolerance; aggravation of porphyria; edema; arthalgias; leg cramps; changes in libido; urticaria, angioedema, anaphylactoid/anaphylactic reactions; hypocalcemia; exacerbation of asthma; increased triglycerides.

OVERDOSAGE

Serious ill effects have not been reported following acute ingestion of large doses of estrogen-containing drug products by young children. Overdosage of estrogen may cause nausea and vomiting, and withdrawal bleeding may occur in females.

DOSAGE AND ADMINISTRATION

When estrogen is prescribed for a postmenopausal woman with a uterus, a progestin should also be initiated to reduce the risk of endometrial cancer. A woman without a uterus does not need progestin. Use of estrogen, alone or in combination with a progestin, should be with the lowest effective dose and for the shortest duration consistent with treatment goals and risks for the individual woman. Patients should be reevaluated periodically as clinically appropriate (e.g., 3-month to 6-month intervals) to determine if treatment is still necessary (See Boxed Warnings and WARNINGS .) For women who have a uterus, adequate diagnostic measures, such as endometrial sampling, when indicated, should be undertaken to rule out malignancy in cases of undiagnosed persistent or recurring abnormal vaginal bleeding.

Patients should be started at the lowest dose.

1. Given cyclically for short term use only:

For treatment of moderate to severe vasomotor symptoms, or moderate to severe symptoms of vulvar and vaginal atrophy associated with the menopause.

Administration should be cyclic (e.g., 3 weeks on and 1 week off).

USUAL DOSAGE RANGES:

Vasomotor symptoms – 1.25 mg daily. If the patient has not menstruated within the last 2 months or more, cyclic administration is started arbitrarily. If the patient is menstruating, cyclic administration is started on day 5 of bleeding.

Moderate to severe symptoms of vulvar and vaginal atrophy – 0.3 mg to 1.25 mg or more daily, depending upon the tissue response of the individual patient. Administer cyclically.

2. Given cyclically:

Female hypogonadism; female castration; primary ovarian failure.

USUAL DOSAGE RANGES:

Female hypogonadism – 2.5 to 7.5 mg daily, in divided doses for 20 days, followed by a rest period of 10 days' duration. If bleeding does not occur by the end of this period, the same dosage schedule is repeated. The number of courses of estrogen therapy necessary to produce bleeding may vary depending on responsiveness of the endometrium. If bleeding occurs before the end of the 10 day period, begin a 20 day estrogen-progestin cyclic regimen with Menest (esterified estrogens tablets), 2.5 to 7.5 mg daily in divided doses, for 20 days. During the last 5 days of estrogen therapy, give an oral progestin. If bleeding occurs before this regimen is concluded, therapy is discontinued and may be resumed on the fifth day of bleeding.

Female castration and primary ovarian failure – 1.25 mg daily, cyclically. Adjust dosage upward or downward according to severity of symptoms and response of the patient. For maintenance, adjust dosage to lowest level that will provide effective control.

3. Given chronically:

Inoperable progressing prostatic cancer — 1.25 to 2.5 mg three times daily. The effectiveness of therapy can be judged by phosphatase determinations as well as by symptomatic improvement of the patient.

Inoperable progressing breast cancer in appropriately selected men and postmenopausal women. (See INDICATIONS AND USAGE) – Suggested dosage is 10 mg three times daily for a period of at least 3 months.

Treated patients with an intact uterus should be monitored closely for signs of endometrial cancer and appropriate diagnostic measures should be taken to rule out malignancy in the event of persistent or recurring abnormal vaginal bleeding. The lowest effective dose of Menest has not been determined.

HOW SUPPLIED

Tablets:

0.3 mg yellow, film-coated oblong tablet imprinted with M72

100's: NDC 61570-072-01

0.625 mg orange, film-coated oblong tablet imprinted with M73

100's: NDC 61570-073-01

1.25 mg green, film-coated oblong tablet imprinted with M74

100's: NDC 61570-074-01

2.5 mg pink, film-coated oblong tablet imprinted with M75

50's: NDC 61570-075-50

STORAGE AND HANDLING

Do not store above 25°C (77°F).

This product's label may have been updated. For current full prescribing information, please visit www.pfizer.com.

LAB 1138–2.0

Revised: 2/2024

PATIENT INFORMATION

Menest ®

(esterified estrogens tablets, USP)

Read this PATIENT INFORMATION before you start taking Menest and read what you get each time you refill Menest. There may be new information. This information does not take the place of talking to your healthcare provider about your medical condition or your treatment.

What is the most important information I should know about Menest (an estrogen hormone)?

- Estrogens increase the chances of getting cancer of the uterus. Report any unusual vaginal bleeding right away while you are taking estrogens. Vaginal bleeding after menopause may be a warning sign of cancer of the uterus (womb). Your healthcare provider should check any unusual vaginal bleeding to find out the cause.
- Do not use estrogens with or without progestins to prevent heart disease, heart attacks, or strokes.
  Using estrogens with or without progestins may increase your chances of getting heart attacks, strokes, breast cancer, and blood clots. Using estrogens with progestins may increase your risk of dementia. You and your healthcare provider should talk regularly about whether you still need treatment with Menest.

What is Menest?

Menest is a medicine that contains estrogen hormones.

What is Menest used for?

Menest is used after menopause to:

- reduce moderate to severe hot flashes. Estrogens are hormones made by a woman's ovaries. The ovaries normally stop making estrogens when a woman is between 45 to 55 years old. This drop in the body estrogen levels causes the "change of life" or menopause (the end of monthly menstrual periods). Sometimes, both ovaries are removed during an operation before natural menopause takes place. This sudden drop in estrogen levels causes "surgical menopause."

When the estrogen levels begin dropping, some women develop very uncomfortable symptoms, such as feelings of warmth in the face, neck, and chest, or sudden strong feelings of heat and sweating ("hot flashes" or "hot flushes"). In some women, the symptoms are mild, and they will not need estrogens. In other women, symptoms can be more severe. You and your healthcare provider should talk regularly about whether you still need treatment with Menest.

- treat moderate to severe dryness, itching, and burning in and around the vagina. You and your healthcare provider should talk regularly about whether you still need treatment with Menest to control these problems. If you use Menest only to treat your dryness, itching, and burning in and around your vagina, talk with your healthcare provider about whether a topical vaginal product would be better for you.
- treat certain conditions in women before menopause if their ovaries do not make enough estrogen naturally.
- ease symptoms of certain cancers that have spread through the body, in men and women.

Who should not take Menest?

Do not start taking Menest if you:

- have unusual vaginal bleeding.
- currently have or have had certain cancers. Estrogens may increase the chances of getting certain types of cancers, including cancer of the breast or uterus. If you have or had cancer, talk with your healthcare provider about whether you should take Menest.
- had a stroke or heart attack in the past year.
- currently have or have had blood clots.
- currently have or have had liver problems.
- are allergic to Menest or any of its ingredients. See the end of this leaflet for a list of ingredients in Menest.
- think you may be pregnant.

Tell your healthcare provider:

- if you are breastfeeding. The hormone in Menest can pass into your milk.
- about all of your medical problems. Your healthcare provider may need to check you more carefully if you have certain conditions, such as asthma (wheezing), epilepsy (seizures), migraine, endometriosis, lupus, problems with your heart, liver, thyroid, kidneys, or have high calcium levels in your blood.
- about all of the medicines you take. This includes prescription and nonprescription medicines, vitamins, and herbal supplements. Some medicines may affect how Menest works. Menest may also affect how your other medicines work.
- if you are going to have surgery or will be on bed rest. You may need to stop taking estrogens.

How should I take Menest?

Your healthcare provider will select the lowest appropriate dose of Menest, determine how frequently it will be taken, and determine the length of time you will be treated, depending on your condition.

For treatment of postmenopausal symptoms, the lowest dose that will control symptoms will be selected and used for the shortest amount of time.

In general, you will take Menest for several weeks, skip a week, and then begin taking Menest again. Again, your healthcare provider will discuss with you the instructions for taking Menest.

If you miss a dose, take it as soon as possible. However, if it is almost time for your next dose, skip the missed dose, and go back to your normal schedule. Do not take 2 doses at the same time.

Estrogens should be used only as long as needed. You and your healthcare provider should talk regularly (for example, every 3 to 6 months) about whether you still need treatment with Menest.

What are the possible side effects of estrogens?

Less common but serious side effects include:

- Breast cancer
- Cancer of the uterus
- Stroke
- Heart attack
- Blood clots
- Dementia
- Gallbladder disease
- Ovarian cancer

These are some of the warning signs of serious side effects:

- Breast lumps
- Unusual vaginal bleeding
- Dizziness and faintness
- Changes in speech
- Severe headaches
- Chest pain
- Shortness of breath
- Pains in your legs
- Changes in vision
- Vomiting

Call your healthcare provider right away if you get any of these warning signs, or any other unusual symptom that concerns you.

Common side effects include:

- Headache
- Breast pain
- Irregular vaginal bleeding or spotting
- Stomach/abdominal cramps, bloating
- Nausea and vomiting
- Hair loss

Other side effects include:

- High blood pressure
- Liver problems
- High blood sugar
- Fluid retention
- Enlargement of benign tumors of the uterus ("fibroids")
- Vaginal yeast infection

These are not all the possible side effects of Menest. For more information, ask your healthcare provider or pharmacist.

What can I do to lower my chances of a serious side effect with Menest?

- Talk with your healthcare provider regularly about whether you should continue taking Menest. If you have a uterus, talk to your healthcare provider about whether the addition of a progestin is right for you.
- See your healthcare provider right away if you get vaginal bleeding while taking Menest.
- Have a breast exam and mammogram (breast X-ray) every year unless your healthcare provider tells you something else. If members of your family have had breast cancer or if you have ever had breast lumps or an abnormal mammogram, you may need to have breast exams more often.
- If you have high blood pressure, high cholesterol (fat in the blood), diabetes, are overweight, or if you use tobacco, you may have higher chances for getting heart disease. Ask your healthcare provider for ways to lower your chances for getting heart disease.

General information about safe and effective use of Menest.

Medicines are sometimes prescribed for conditions that are not mentioned in patient information leaflets. Do not take Menest for conditions for which it was not prescribed. Do not give Menest to other people, even if they have the same symptoms you have. It may harm them. Keep Menest out of the reach of children.

This leaflet provides a summary of the most important information about Menest. If you would like more information, talk with your healthcare provider or pharmacist. You can ask for more information about Menest that is written for health professionals.

What are the ingredients in Menest?

Menest is a mixture of esterified estrogens that are of the type excreted by pregnant mares. Menest also contains ethyl cellulose, fragrances, hydroxypropyl cellulose, hypromellose 2910, lactose, magnesium stearate, methylcellulose, polyethylene glycol, sodium bicarbonate, shellac, starch, stearic acid, titanium dioxide, and vanillin. The tablets come in different strengths; the color ingredients for each strength are:

0.3 mg Tablet: FD&C Yellow No. 6, D&C Yellow No. 10.

0.625 mg Tablet: FD&C Yellow No. 6, D&C Yellow No. 10.

1.25 mg Tablet: FD&C Yellow No. 6, D&C Yellow No. 10, and FD&C Blue No. 1.

2.5 mg Tablet: D&C Red No. 30.

How should I store Menest?

Do not store above 25°C (77°F).

This product's label may have been updated. For current full prescribing information, please visit www.pfizer.com.

LAB 1139-1.0

Revised: 4/2019

PRINCIPAL DISPLAY PANEL - 0.3 mg Tablet Bottle Label

Pfizer

NDC 61570-072-01

Menest®
(esterified estrogens
tablets, USP)

0.3 mg

100 Tablets
Rx only

PRINCIPAL DISPLAY PANEL - 0.625 mg Tablet Bottle Label

Pfizer

NDC 61570-073-01

Menest®
(esterified estrogens
tablets, USP)

0.625 mg

100 Tablets
Rx only

PRINCIPAL DISPLAY PANEL - 1.25 mg Tablet Bottle Label

Pfizer

NDC 61570-074-01

Menest®
(esterified estrogens
tablets, USP)

1.25 mg

100 Tablets
Rx only

PRINCIPAL DISPLAY PANEL - 2.5 mg Tablet Bottle Label

Pfizer

NDC 61570-075-50

Menest®
(esterified estrogens
tablets, USP)

2.5 mg

50 Tablets
Rx only